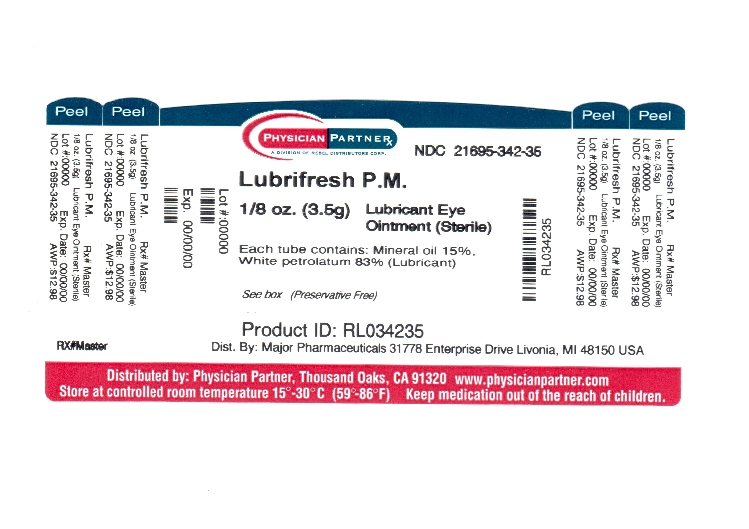 DRUG LABEL: LubriFresh P.M.
NDC: 21695-342 | Form: OINTMENT
Manufacturer: Rebel Distributors Corp
Category: otc | Type: HUMAN OTC DRUG LABEL
Date: 20120124

ACTIVE INGREDIENTS: MINERAL OIL 150 mg/1 g; PETROLATUM 830 mg/1 g
INACTIVE INGREDIENTS: LANOLIN

Artificial Tears Ointment Drug Facts

Active ingredient

Mineral oil 15%
White petrolatum 83%

Purpose

Lubricant

Uses

- to prevent further irritation
- to relieve dryness of the eye

Warnings

When using this product

- replace cap after use
- do not touch tip of container to any surface to avoid contamination

Stop use and ask a doctor if

- condition worsens or persists for more than 72 hours
- you experience eye pain, changes in vision, continued redness or irritation of the eye

Keep out of reach of children.

If swallowed, get medical help or contact a Poison Control Center right away.

Directions

pull down the lower lid of the affected eye (s)
apply a small amount (1/4 inch) of ointment to the inside of eyelid
apply one or more times daily or as directed by a doctor

Other information

- store at 15° - 30°C (59° - 86°F)
- keep tightly closed
- see crimp of tube or carton for Lot Number and Expiration Date

Inactive ingredient

lanolin oil

Questions or comments?

Serious side effects associated with use of this product may be reported to 1800-323-0000

*Major LubriFreshTM P.M. is not manufactured or distributed by Allergan Inc., distributor of Refresh P.M.®